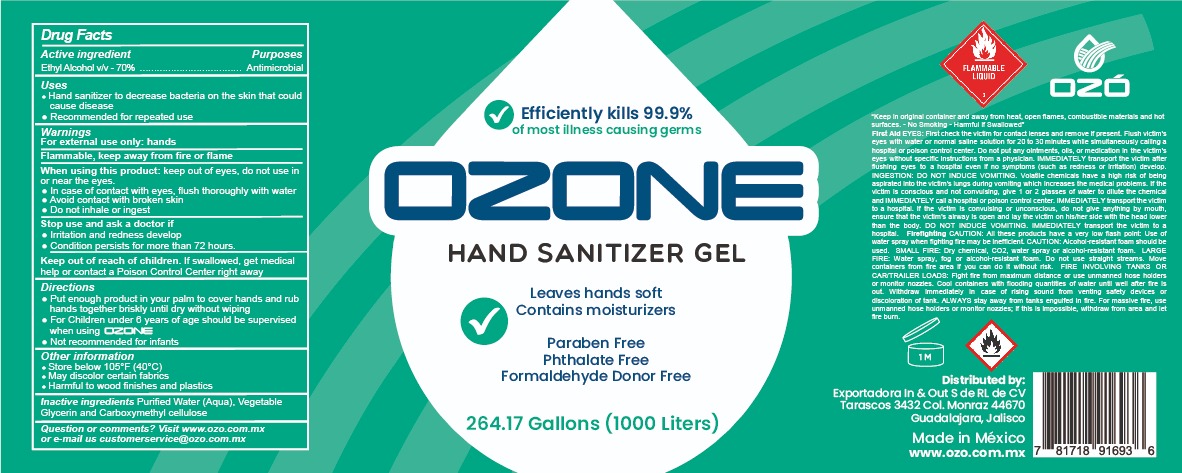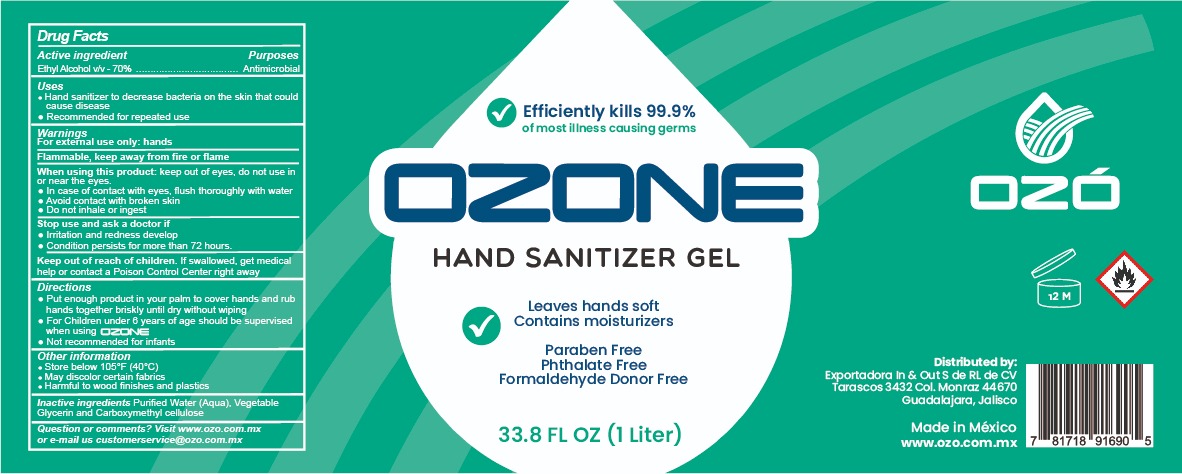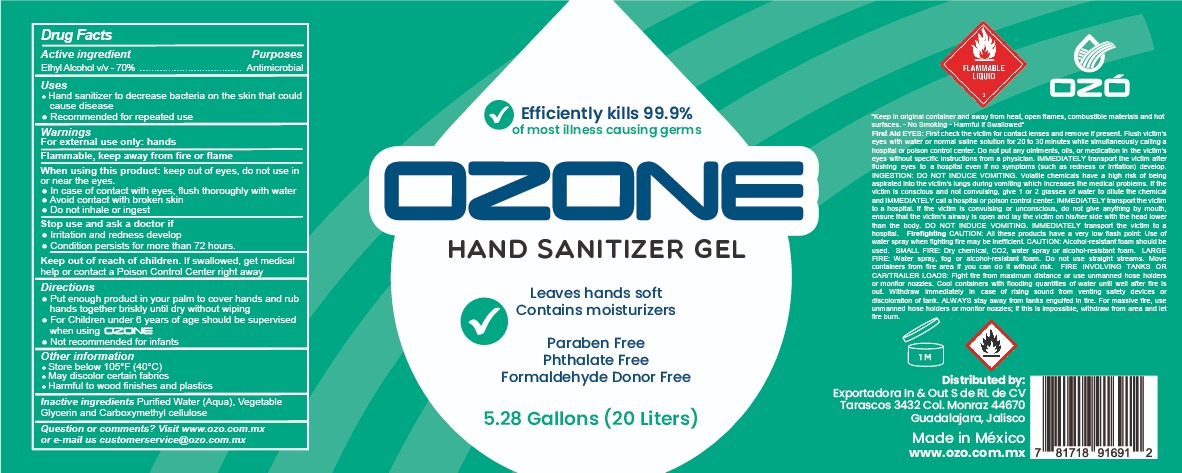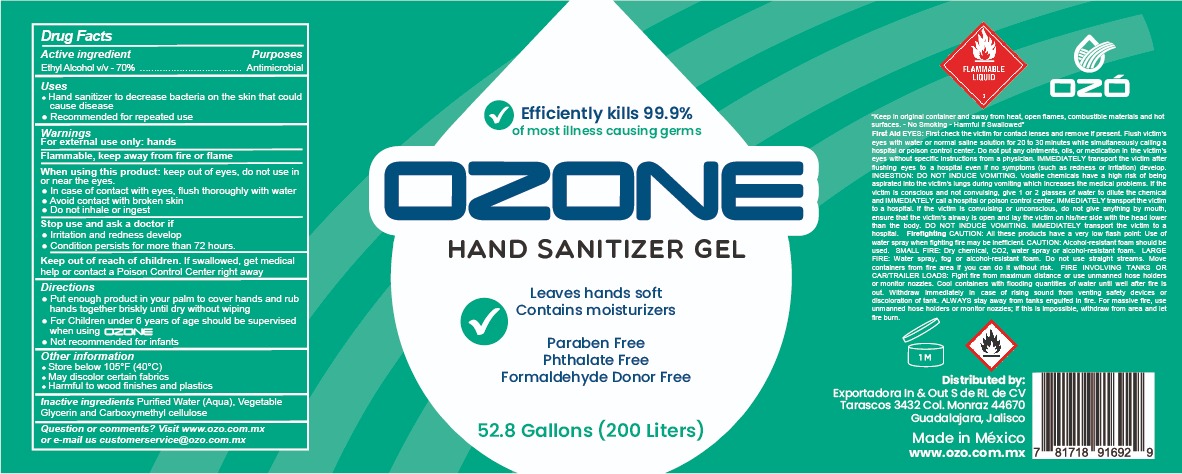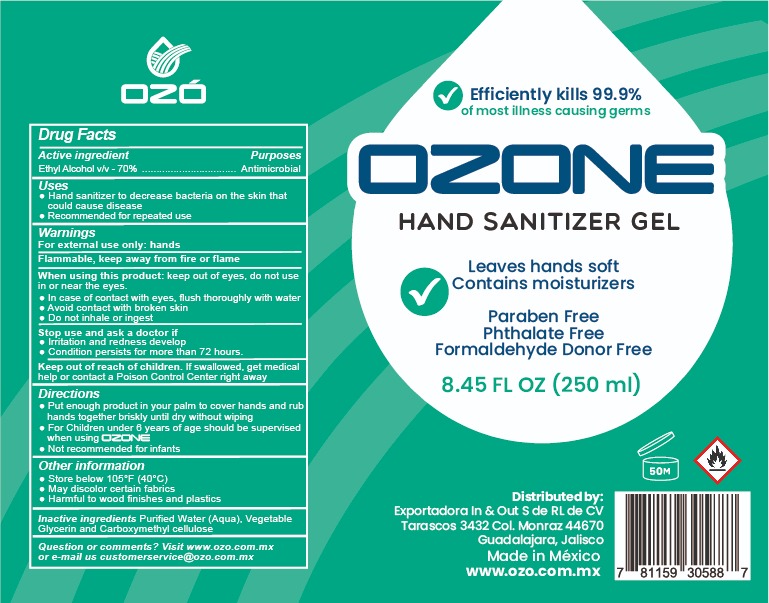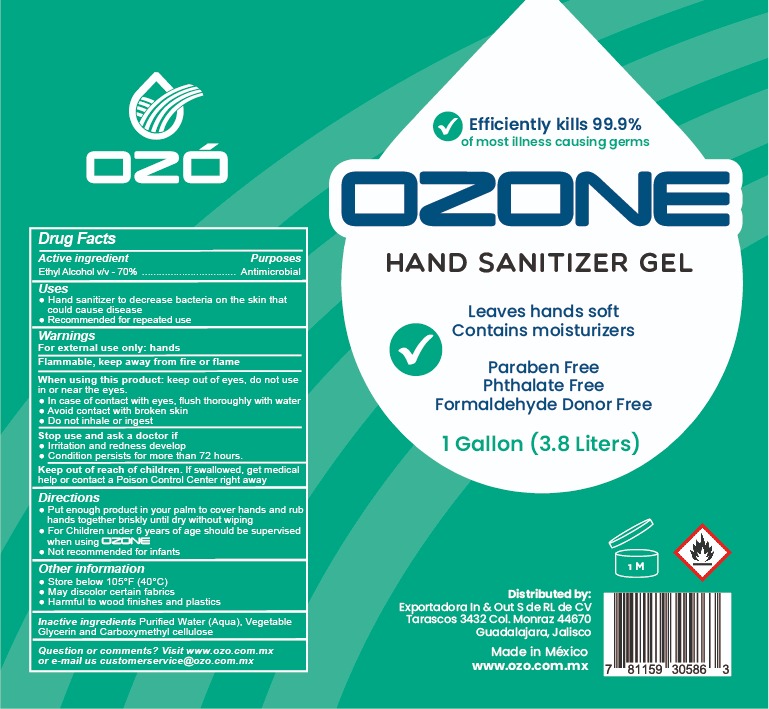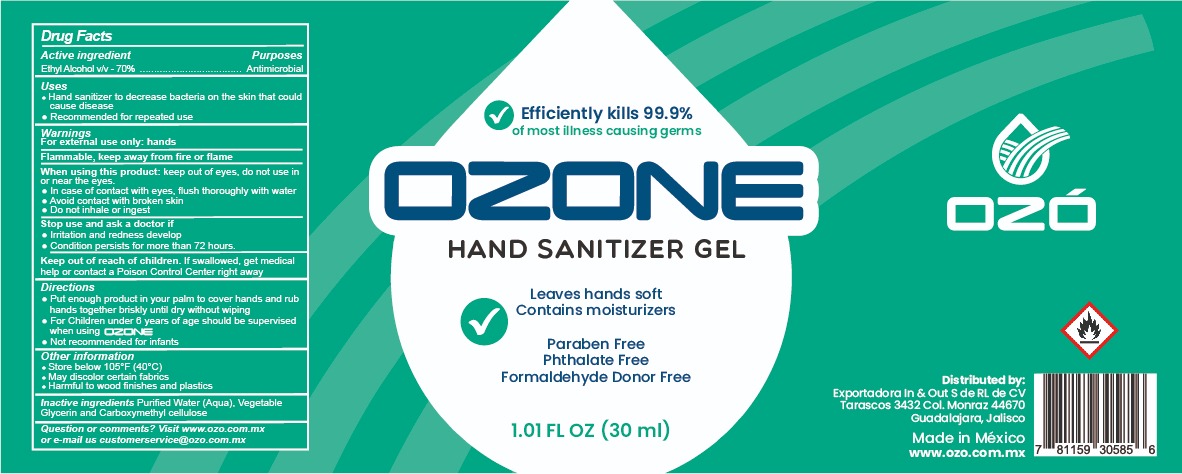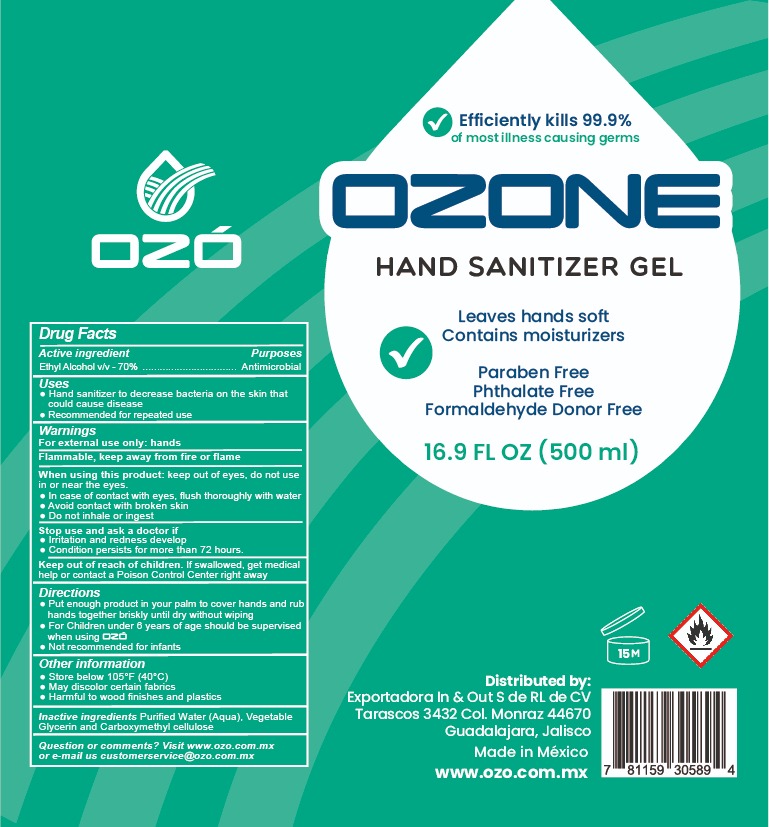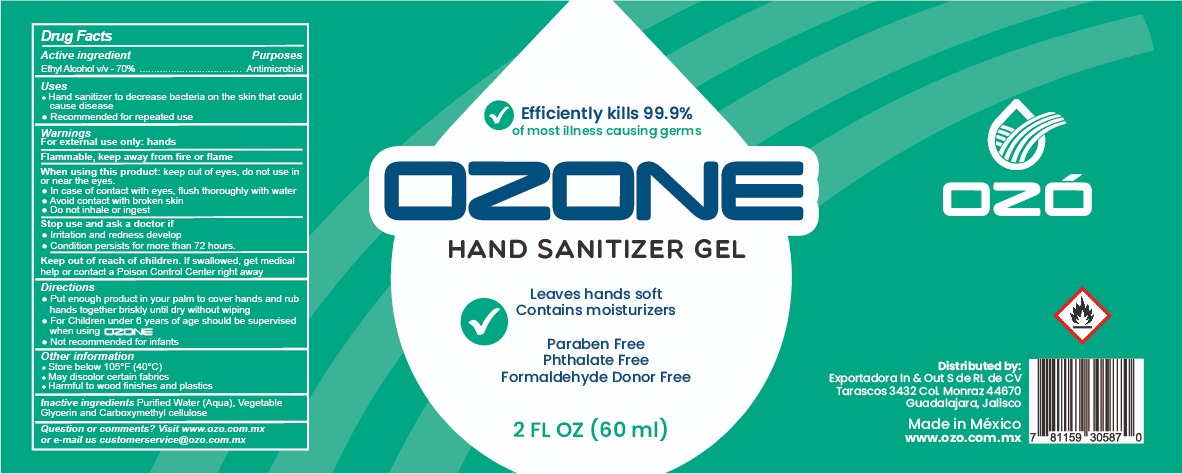 DRUG LABEL: HAND SANITIZER
NDC: 77210-0002 | Form: GEL
Manufacturer: EXPORTADORA IN & OUT S DE RL DE CV
Category: otc | Type: HUMAN OTC DRUG LABEL
Date: 20200618

ACTIVE INGREDIENTS: ALCOHOL 70 mL/100 mL
INACTIVE INGREDIENTS: WATER; GLYCERIN 3.2 mL/100 mL; CARBOXYMETHYLCELLULOSE 5 mL/100 mL

Active Ingredient

Ethyl Alcohol v/v 70%

Purposes

Antimicrobial

Uses

-Hand sanitizer to decrease virus and bacteria on the skin that could cause diseases

-Recommended for repeated use

Warnings

For external use only: hands

Flammable, keep away from fire or flame

When use this product

keep out of eyes, do not use in or near the eyes.

In case of contact eye flush thorougly with water

avoid contact with broken skin

do not inhale or ingest

When using this product

Keep out of eyes, do not use in or near the eyes

Stop use and ask a doctor if

irritation and redness develop

condition persist for more than 72 hours. Keep out reach of children. If swallowed, get medical help or contact Poison Control Center right away

keep out of reach of children

if swallowed, get medical help or contact a Poison Center right away

Directions

-Put enough product in your palm to cover hands and rub hands together briskly until dry out without wiping

-For children under 6 years of age should be supervised when using OZO

-Not recommended for infants

Other information

Store below 105 F (40C)

May discolor certain fabrics

Harmful to wood finishes and plastics

Inactive ingredients

Purified water (aqua), Vegetable Glycerin and carboxymethyl cellulose

Question o comments?

Visit www.ozo.com.mx or e-mail us customerservice@ozo.com.mx

For the 20 lt, 200lt and 1000lt label

Keep in original container an away form heat, open flames, combustible materials and hot surfaces, no smoking,- Harmful is Swallowed"

First aid: first check the victim for contact eyes lenses and removes if presents. Flush victim's eye with water or normal saline solution for 20 to 30 minutes while simultaneoulsy calling a hospital or poison control center, Do not put any oinments, oils, medication in the victim's eye without specific instructions from a physician.

IMMEDIATELY transport the victim after flushing eyes to a hospital even if no symptoms (such as redness or irritation) develop.

INGESTION: DO NOT INDUCE VOMIT. Volatile chemicals have a high risk of being aspirated into the victims lungs during vomiting wich increase the medical problems. If the victim is conscious and not convulsing, give 1 or 2 glasses of water to dilute the chemical and IMMEDIATLY transport the victim to a hospital. If the victim is convulsing or unconscious, do not give anything by mouth, ensure that the victims airway is open and lay the victim on his/her side with the head lower than the body. DO NOT INDUCE VOMITING. IMMEDIATLY transport the victim to a hospital:

Firefighting CAUTION: all these products have a very low flash point: use water spray when fighting fire may be inefficient: CAUTION: Alcohol-resistant foam should be used.SMALL FIRE: Dry Chemicals, co2, water spray or alcohol-resistant foam. LARGE FIRE: Water spray, fog or alcohol resistant foam. Do not use straight streams. Move containers from fire area if you can do it without risk. FIRE INVOLVING TANKS OR CAR/TRAILERS LOADS: Fight fire for maximun distance or use unmanned hose holders or monito nozzles: Cool containers with flooding quiantities of water until well after fire is out. Withdraw immediatly in case of rising sounf from venting safety devices or discoloration of thank. ALWAYS stay away from tanks engulfed in fire. For massive fire, use unmaned hose holders or monitor nozzles; if this is imposible. Withdraw from area and let the fire burn.

Principal display

efiiciently kills 99.9%

of most illness causing germs

ozone

hand sanitizer gel

leaves hands soft

contains moisturizers

paraben free

phthalate free

formaldehyde Donor Free